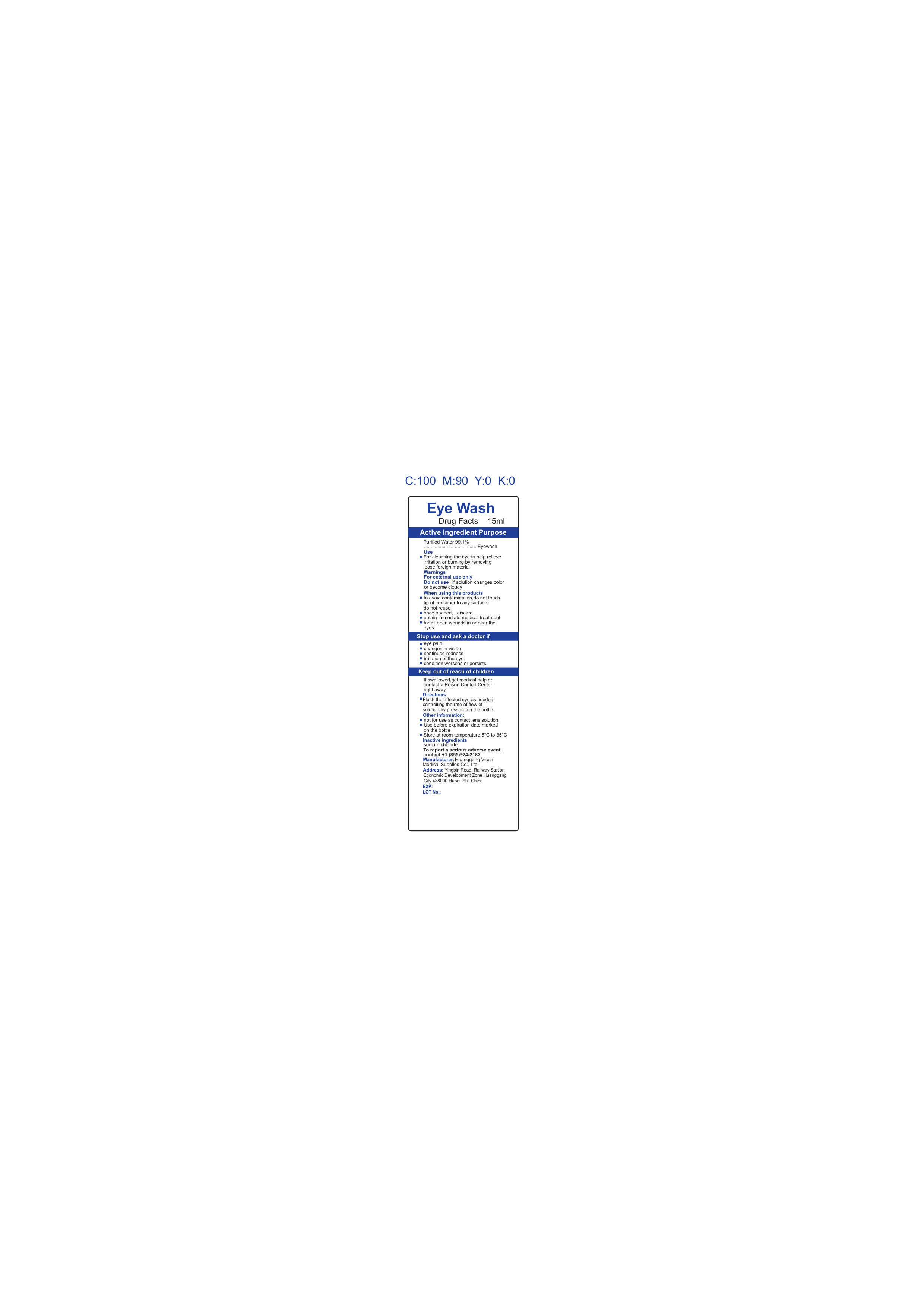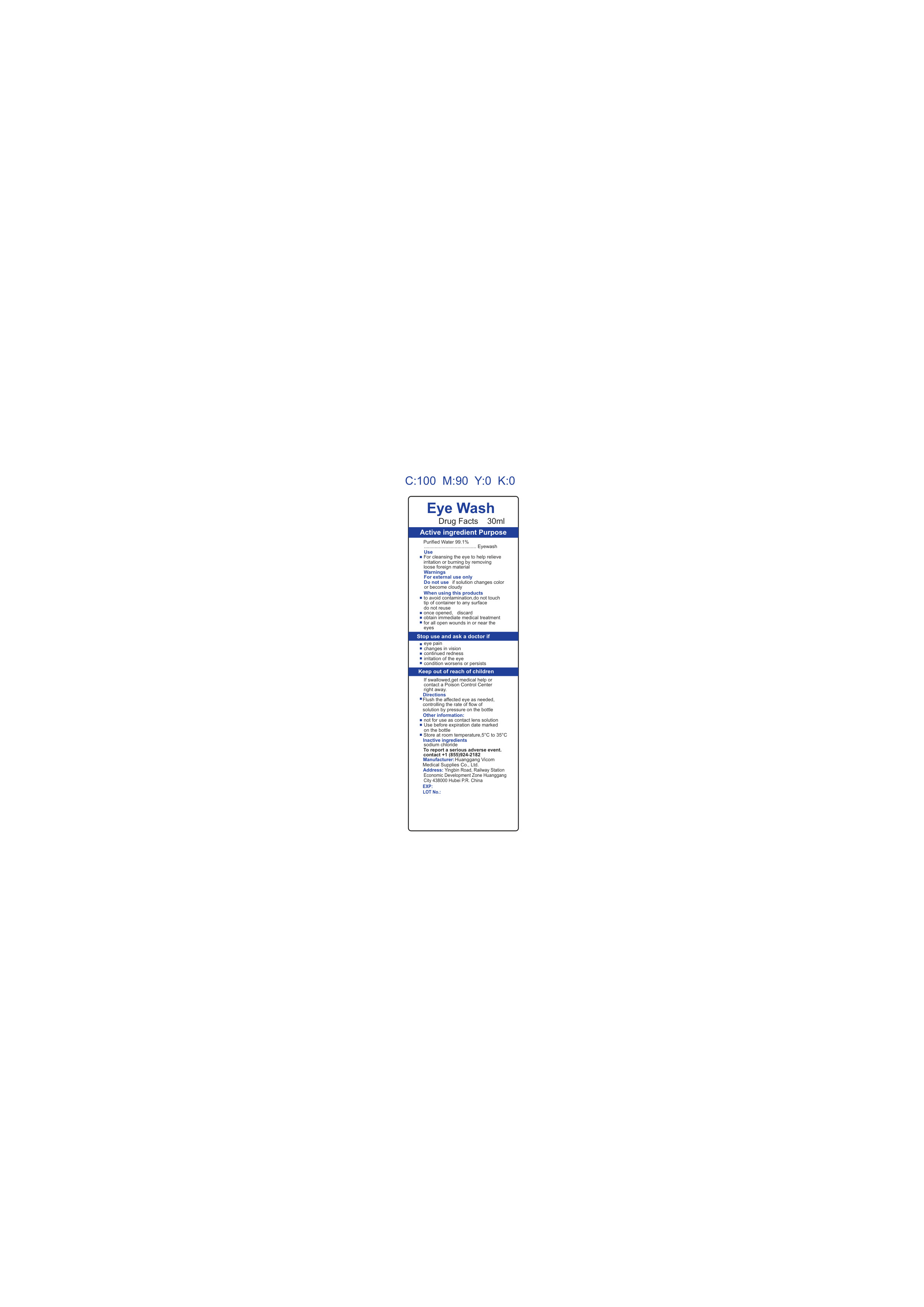 DRUG LABEL: Huanggang Eye Wash
NDC: 85426-002 | Form: LIQUID
Manufacturer: Huanggang Vicom Medical Supplies Co., Ltd.
Category: otc | Type: HUMAN OTC DRUG LABEL
Date: 20250406

ACTIVE INGREDIENTS: WATER 99 mL/100 mL
INACTIVE INGREDIENTS: SODIUM CHLORIDE 1 mL/100 mL

Eye Wash Huanggang Vicom Medical Supplies Co.,

ACTIVE INGREDIENT

Purified water (99.1%)

ASK DOCTOR

Eye Pain

Changes In Vision

Continued Redness

Irritation in the Eye

Condition Worsens or persists

PURPOSE

Eye Wash

INSTRUCTIONS FOR USE

To pour - hold bottle securely, twist off top to remove
Control rate of flow by pressure on the bottle
Flush the affected eye(s) as needed
Do not touch bottle tip to eye
If necessary, continue flushing with emergency eyewash or shower.

Do not use if pack is damaged

Do not use resterilize and reuse

DOSAGE AND ADMINISTRATION

Topical irrigation solution

0.9% w/v Sodium Chloride

INDICATIONS AND USAGE

For topical irrigation of eyes, burns and wounds

INACTIVE INGREDIENT

0.9% w/v Sodium Chloride

OTHER SAFETY INFORMATION

Caution:

Discard any unused solution

Single use only

STORAGE AND HANDLING

Store in cool dry place

Keep out of direct sunlight

Keep out of reach of children

Keep out of reach of children

15 mL Label

30 mL Label